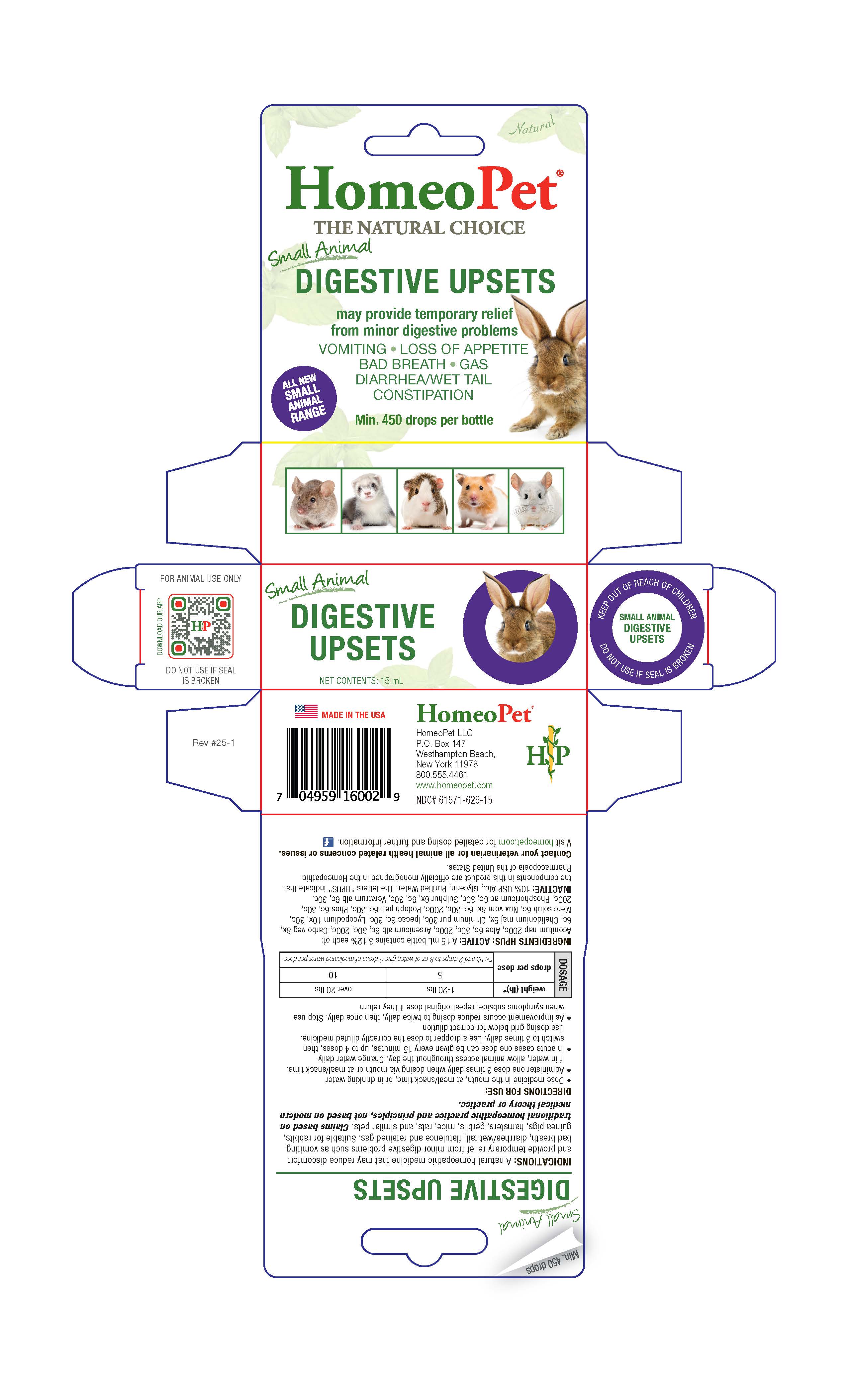 DRUG LABEL: Digestive Upsets
NDC: 61571-626 | Form: LIQUID
Manufacturer: HomeoPet, LLC
Category: homeopathic | Type: OTC ANIMAL DRUG LABEL
Date: 20251216

ACTIVE INGREDIENTS: ACONITUM NAPELLUS 200 [hp_C]/15 mL; ALOE FEROX LEAF 6 [hp_C]/15 mL; ARSENIC TRIOXIDE 6 [hp_C]/15 mL; ACTIVATED CHARCOAL 8 [hp_X]/15 mL; CHELIDONIUM MAJUS 5 [hp_X]/15 mL; QUININE ARSENITE 30 [hp_C]/15 mL; IPECAC 6 [hp_C]/15 mL; LYCOPODIUM CLAVATUM SPORE 10 [hp_X]/15 mL; MERCURIUS SOLUBILIS 6 [hp_C]/15 mL; STRYCHNOS NUX-VOMICA SEED 8 [hp_X]/15 mL; PODOPHYLLUM PELTATUM ROOT 6 [hp_C]/15 mL; PHOSPHORUS 6 [hp_C]/15 mL; PHOSPHORIC ACID 6 [hp_C]/15 mL; SULFUR 6 [hp_X]/15 mL; VERATRUM ALBUM ROOT 6 [hp_C]/15 mL
INACTIVE INGREDIENTS: ALCOHOL; WATER; GLYCERIN

Digestive Upsets

Small Animal Digestive Upsets

may provide temporary relief from minor digestive problems

VOMITING-LOSS OF APPETITE-BAD BREATH

GAS-DIARRHEA/WET TAIL-CONSTIPATION

Directions for Use and Dosage

- Dose medicine in the mouth, at meal/snack time, or in drinking water
- Administer one dose 3 times daily when dosing via mouth or at meal/snack time. If in water, allow animal acess throughout the day. Change water daily
- In acute cases one dose can be given every 15 minutes, up to 4 doses, then switch to 3 times daily. Use a dropper to dose the correctly diluted medicine. Use dosing grid below for correct dilution
- As improvement occurs reduce dosing to twice daily, then once daily. Stop use when symptoms subside; repeat original dose if they return

Dosage | weight (lb)* | 1-20 lbs | over 20 lbs
Dosage | drops per dose | 5 | 10
Dosage | drops per dose | *<1 lb add 2 drops to 8 oz of water, give 2 drops of medicated water per dose

Contact veterianarian

Contact your veterinarian for all animal health related concerns or issues.

Visit homeopet.com for detailed dosing and further information.

Ingredients HPUS: Active

Acontinum nap 200c, Aloe 6c, 30c, 200c, Arsenicum alb 6c, 30c, 200c, Carbo veg 8x, 6c, Chelidonium maj 5x, Chininum pur 30c, Ipecac 6c, 30c, Lycopodium 10x, 30c, Merc solub 6c, Nux vom 8x, 6c, 30c, 200c, Podoph pelt 6c, 30c, Phos 6c, 30c, 200c, Phosphoricum ac 6c, 30c, Sulphur 6x, 6c, 30c, Veratrum alb 6c, 30c.

Inactive Ingredients

USP Alcohol, Glycerin, Purified Water

Indications

A natural homeopathic medicine that may reduce discomfort and provide temporary relief from minor digestive problems such as vomiting, bad breath, diarrhea/wet tail, flatulence and retained gas. Suitable for rabbits, guinea pigs, hamsters , gerbils, mice, rats, and similar pets. Claims based on traditional homeopathic practice and principles, not based on modern medical theory or practice.